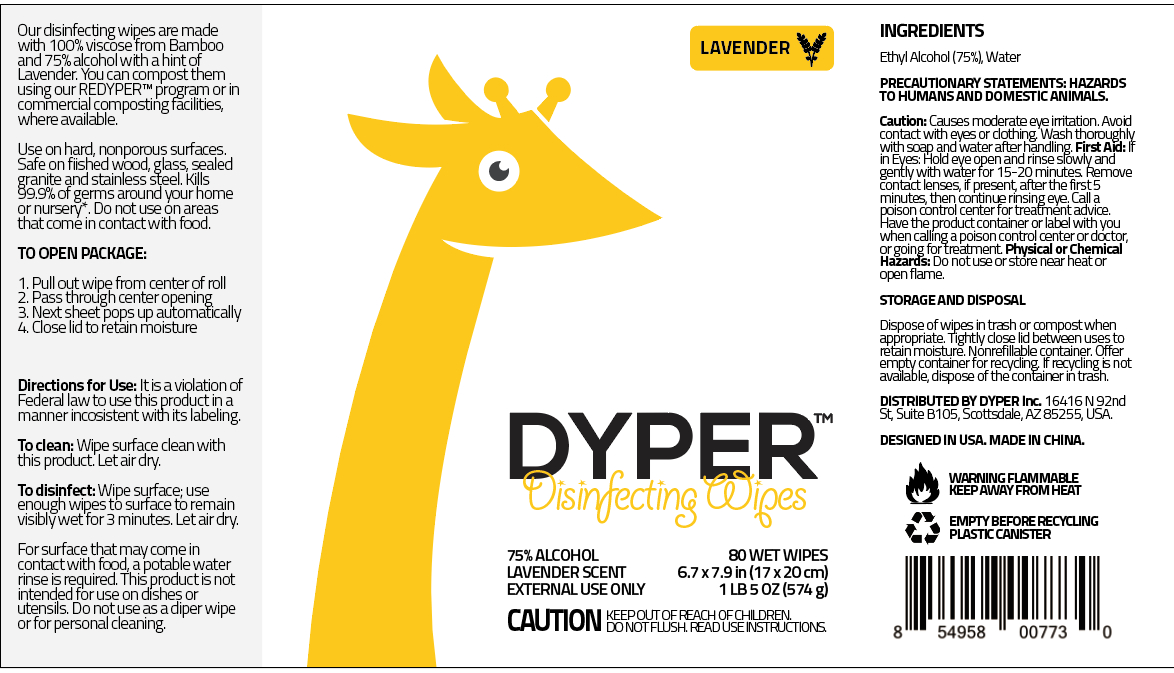 DRUG LABEL: DISINFECTING WIPES
NDC: 55415-003 | Form: CLOTH
Manufacturer: JIANGSU MEIFAN BIOTECHNOLOGY CO., LTD.
Category: otc | Type: HUMAN OTC DRUG LABEL
Date: 20220422

ACTIVE INGREDIENTS: ALCOHOL 100 mL/80 1
INACTIVE INGREDIENTS: FRAGRANCE LAVENDER & CHIA F-153480; WATER

DOSAGE AND ADMINISTRATION

Do notuse or store near heator open flame.

INACTIVE INGREDIENT

SPUNLACE NONWOVEN, PURIFIED WATER, FRAGRANCE

INDICATIONS AND USAGE

1. Pullout wipe from center of roll
2. Pass through center opening,
3. Next sheet POPS up automatically
4. Close lid t如o retain moisture Directions for Use: Itis a violation of Federal law to use this productin a manner incosistent with its labeling.

To clean; Wipe surface dleanwith this product. Let air dry.
To disinfect: Wipe suyrface; use enough wipes to surface to remain visiblywetfor 3 minutes.

ACTIVE INGREDIENT

ETHYL ALCOHOL

keep out of children

PURPOSE

Disinfection
Sterilization
No Rinseing

WARNINGS

Causes moderate eye itation. Avoid contact with eyes or dogthing Wash thoroughly with soap and water afterhandling. First Aid: f
in Eyes: Hold eye open and rinse slowly and gentlywith water for 15-20 minutes. Remove Contaict lenses, if present after the first5
minutes, then continue rinsing eye.Do notuse or store near heator open flame.